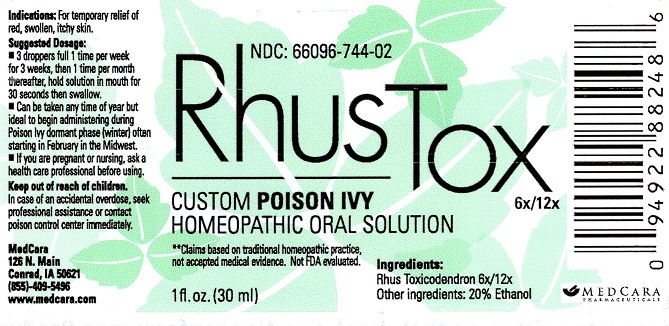 DRUG LABEL: Rhus Tox 6x/12x
NDC: 66096-744 | Form: LIQUID
Manufacturer: OHM PHARMA INC.
Category: homeopathic | Type: HUMAN OTC DRUG LABEL
Date: 20181029

ACTIVE INGREDIENTS: TOXICODENDRON PUBESCENS LEAF 6 [hp_X]/30 mL
INACTIVE INGREDIENTS: ALCOHOL

RHUS TOX 6x/12x

ACTIVE INGREDIENT

Ingredients:

Rhus Toxicodendron 6x/12x

**Claims based on traditional homeopathic practice,

not accepted medical evidence. Not FDA evaluated.

INDICATIONS AND USAGE

Indications: For temporary relief of red, swollen, itchy skin.

Suggested Dosage:

•3 droppers full 1 time per week for 3 weeks, then 1 time per month thereafter, hold solution in mouth for 30 seconds then swallow.

• Can be taken any time of year but ideal to begin administering during Poision Ivy dormant phase (winter) often starting in February

in the Midwest.

WARNINGS

•If you are pregnant or nursing, ask a health care professional before using.

Keep out of reach of children. In case of an accidental overdose, seek professional assistance or contact a poison control center immediately.

Keep out of reach of children.

INACTIVE INGREDIENT

Other ingredients: 20% Ethanol

QUESTIONS

MedCara

126 N. Main

Conrad, IA 50621

(855)-409-5496

www.medcara.com

PACKAGE LABEL

NDC: 66096-744-02

Rhus Tox

6x/12x

CUSTOM POISON IVY

HOMEOPATHIC ORAL SOLUTION

1 fl. oz. (30 ml)

PURPOSE

For temporary relief of red, swollen, itchy skin.